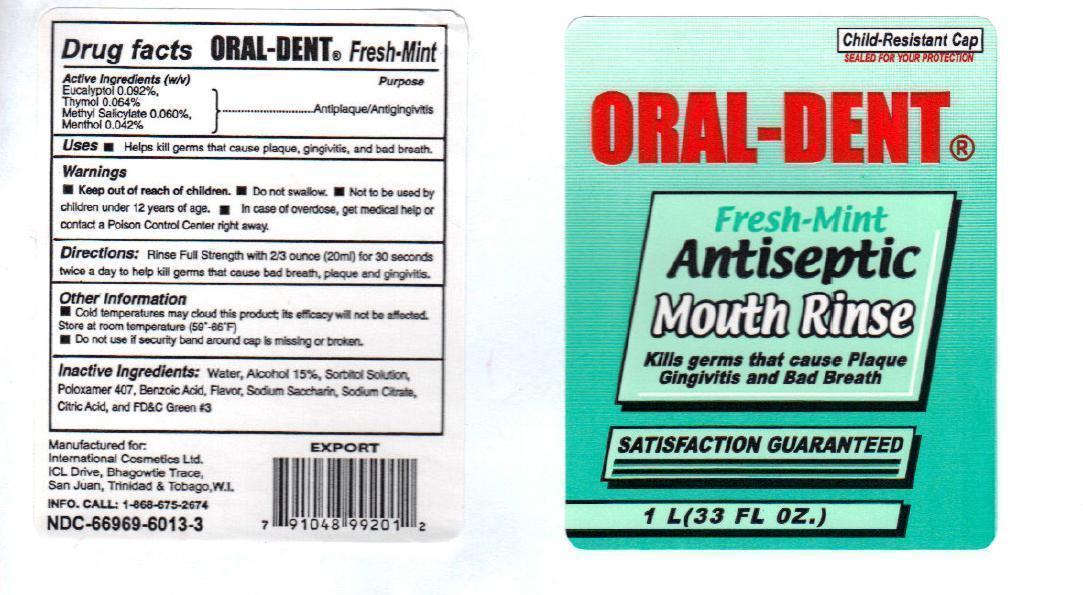 DRUG LABEL: Oral Dent
NDC: 66969-6013 | Form: MOUTHWASH
Manufacturer: International Cosmetics Ltd.
Category: otc | Type: HUMAN OTC DRUG LABEL
Date: 20140314

ACTIVE INGREDIENTS: EUCALYPTOL 0.092 g/100 mL; THYMOL 0.064 g/100 mL; METHYL SALICYLATE 0.060 g/100 mL; MENTHOL 0.042 g/100 mL
INACTIVE INGREDIENTS: WATER; ALCOHOL; SORBITOL; POLOXAMER 407; BENZOIC ACID; SACCHARIN SODIUM; SODIUM CITRATE; CITRIC ACID MONOHYDRATE; FD&C GREEN NO. 3

Oral Dent Fresh Mint

Active ingredients (W/V)

Eucalyptol 0.092%
Thymol 0.064%
Methyl Salicylate 0.060%
Menthol 0.042%

Purpose

Antiplaque/Antigingivitis

Keep out of reach of children.

In case of overdose, get medical help or contact a Poison Control Center right away.

Uses

Helps kill germs that cause plaque, gingivitis and bad breath.

Warnings

- Do not swallow
- Not to be used by children under 12 years of age

Directions

Rinse Full Strength with 2/3 ounce (20 ml) for 30 seconds twice a day to help kill germs that cause bad breath, plaque and gingivitis.

Other information

- Cold temperature may cloud this product; its efficacy will not be affected. Store at room temperature (59^0-86^0 F)

- Do not use if security band around cap is missing or broken

Inactive ingredients

Water, Alcohol (15%), Sorbitol Solution, Poloxamer 407, Benzoic Acid, Flavour, Sodium Saccharin, Sodium Citrate, Citric Acid and FD&C Green No.3.

Manufactured for

International Cosmetics Ltd.

ICL Drive, Bhagowtie Trace,

San Juan, Trinidad & Tobago, W.I.

INFO. CALL:1-868-675-2674